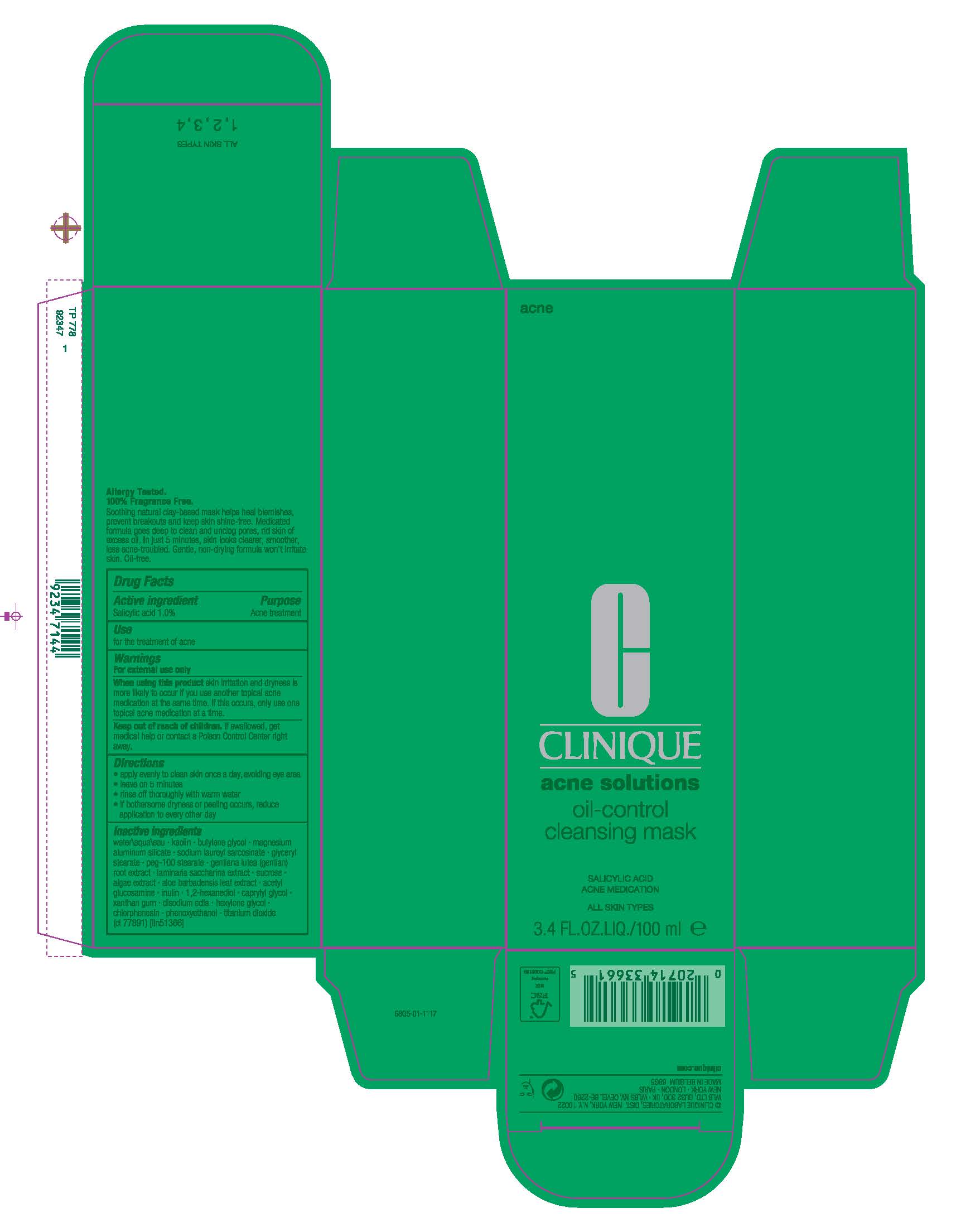 DRUG LABEL: ACNE solutions oil CONTROL CLEANSING MASK
NDC: 49527-713 | Form: CREAM
Manufacturer: CLINIQUE LABORATORIES LLC
Category: otc | Type: HUMAN OTC DRUG LABEL
Date: 20241225

ACTIVE INGREDIENTS: SALICYLIC ACID 10 mg/1 mL
INACTIVE INGREDIENTS: HEXYLENE GLYCOL; WATER; KAOLIN; BUTYLENE GLYCOL; MAGNESIUM ALUMINUM SILICATE; SODIUM LAUROYL SARCOSINATE; GLYCERYL STEARATE CITRATE; PEG-100 STEARATE; GENTIANA LUTEA ROOT; SACCHARINA LATISSIMA; SUCROSE; AGAR, UNSPECIFIED; ALOE; DISODIUM ACETYL GLUCOSAMINE PHOSPHATE; INULIN; 1,2-HEXANEDIOL; XANTHAN GUM; CAPRYLYL GLYCOL; EDETATE DISODIUM; CHLORPHENESIN; TITANIUM DIOXIDE; PHENOXYETHANOL

ACNE SOLUTIONS OIL CONTROL CLEANSING MASK
ACNE MEDICATION ALL SKIN TYPES

Drug Facts

ACTIVE INGREDIENT

Active ingredient | Purpose
Salicylic acid 1.0% | Acne treatment

Use

for the treatment of acne

Warnings

For external use only.

When using this product

- using other topical acne drugs at the same time or right after use of this product may increase dryness or irritation of the skin.
- If this occurs, only one medication should be used unless directed by a doctor

Keep out of reach of children. If swallowed, get medical help or contact a Poison Control Center right away.

Directions

- apply evenly to clean skin, avoiding eye area
- leave on 5 minutes
- rinse off thoroughly with warm water
- If bothersome dryness or peeling occurs, reduce application to every other day

Inactive ingredients

water\aqua\eau , kaolin , butylene glycol , magnesium aluminum silicate , sodium lauroyl sarcosinate , glyceryl stearate , peg-100 stearate , gentiana lutea (gentian) root extract , laminaria saccharina extract , sucrose , algae extract , aloe barbadensis leaf extract , acetyl glucosamine , inulin , 1,2-hexanediol , caprylyl glycol , xanthan gum , disodium edta , hexylene glycol , chlorphenesin , phenoxyethanol , titanium dioxide (ci 77891) <iln51366>

PRINCIPAL DISPLAY PANEL - 100 ml Tube Carton

acne

CLINIQUE
acne solutions

oil-control
cleansing mask

SALICYLIC ACID
ACNE MEDICATION

ALL SKIN TYPES

3.4 FL.OZ.LIQ./100 ml ℮